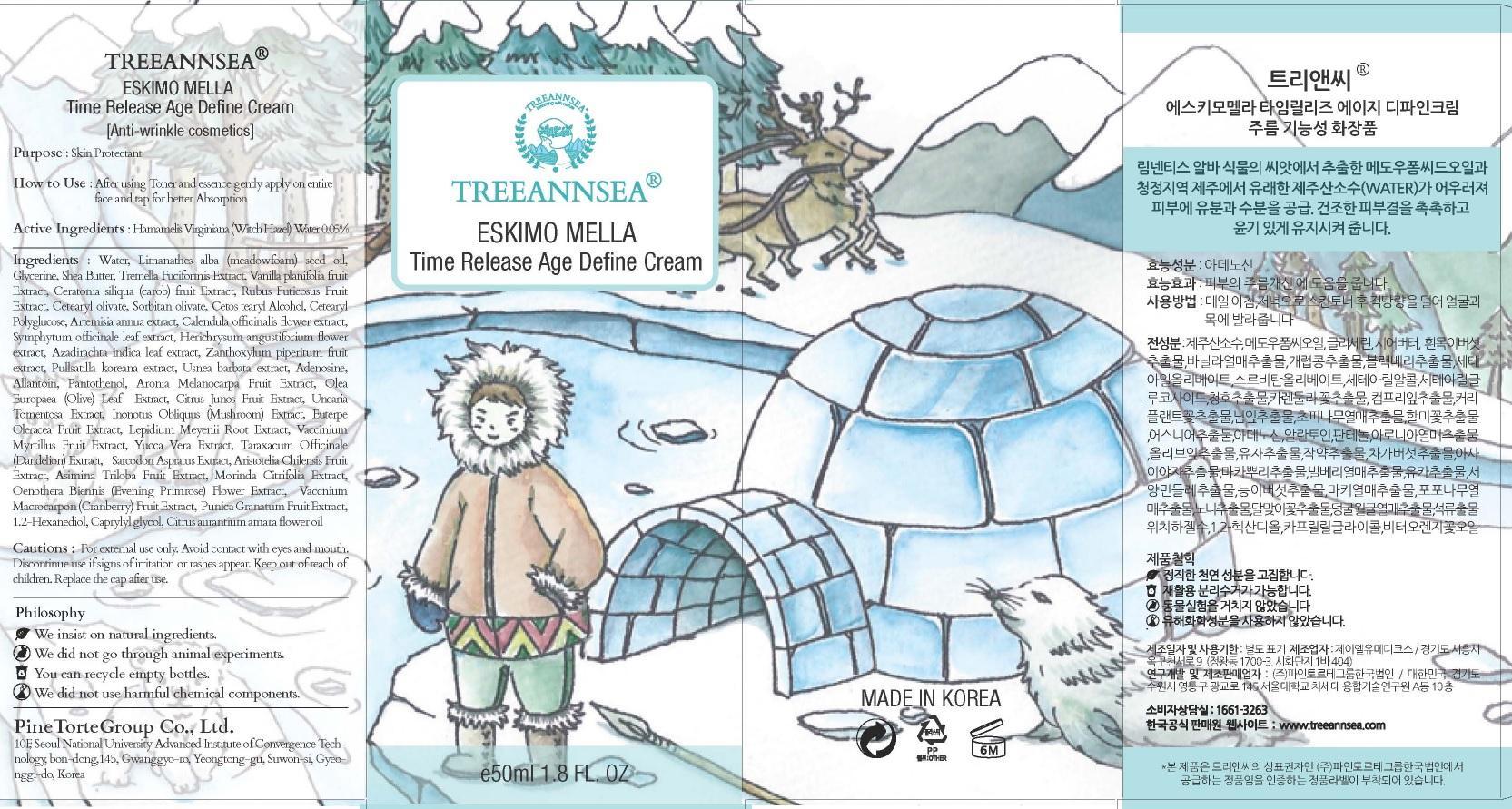 DRUG LABEL: TREEANNSEA ESKIMO MELLA TIME RELEASE AGE DEFINE
NDC: 69515-010 | Form: CREAM
Manufacturer: PINE TORTE GROUP CO., LTD.
Category: otc | Type: HUMAN OTC DRUG LABEL
Date: 20150318

ACTIVE INGREDIENTS: Witch Hazel 0.025 mg/50 mL
INACTIVE INGREDIENTS: Water; Glycerin

ACTIVE INGREDIENT

Active Ingredients: Hamamelis Virginiana (Witch Hazel) Water 0.05%

INACTIVE INGREDIENT

Inactive Ingredients: Water, Limanathes alba (meadowfoam) seed oil, Glycerin, Shea Butter, Tremella Fuciformis Extract, Vanilla planifolia fruit Extract, Ceratonia siliqua (carob) fruit Extract, Rubus Futicosus Fruit Extract, Cetearyl olivate, Sorbitan olivate, Cetostearyl Alcohol, Cetearyl Polyglucose, Artemisia annua extract, Calendula officinalis flower extract, Symphytum officinale leaf extract, Herichrysum angustiforium flower extract, Azadirachta indica leaf extract, Zanthoxylum piperitum fruit extract/Pullsatilla koreana extract, Usnea barbata extract, Adenosine, Allantoin, Pantothenol, Aronia Melanocarpa Fruit Extract, Olea Europaea (Olive) Leaf Extract , Citrus Junos Fruit Extract , Uncaria Tomentosa Extract, Inonotus Obliquus (Mushroom) Extract, Euterpe Oleracea Fruit Extract, Lepidium Meyenii Root Extract, Vaccinium Myrtillus Fruit Extract, Yucca Vera Extract, Taraxacum Officinale (Dandelion) Extract, Sarcodon Aspratus Extract, Aristotelia Chilensis Fruit Extract, Asimina Triloba Fruit Extract, Morinda Citrifolia Extract, Oenothera Biennis (Evening Primrose) Flower Extract, Vaccinium Macrocarpon (Cranberry) Fruit Extract, Punica Granatum Fruit Extract, 1.2-Hexanediol, Caprylyl glycol, Citrus aurantium amara flower oil

PURPOSE

Purpose: Skin Protectant

Cautions

Cautions: For external use only. Avoid contact with eyes and mouth. Discountinue use if signs of irritation or rashes appear. Keep out of reach of children. Replace the cap after use.

KEEP OUT OF REACH OF CHILDREN

INDICATIONS & USAGE

How to use: After using Toner and Essence gently apply on entire face and tap for better absorption.

DOSAGE & ADMINISTRATION

How to use: After using Toner and Essence gently apply on entire face and tap for better absorption.